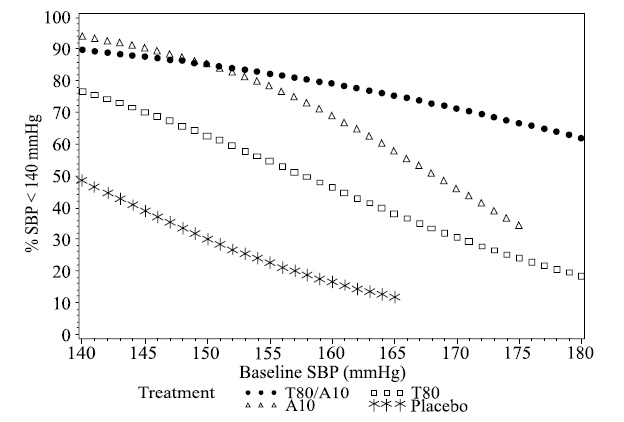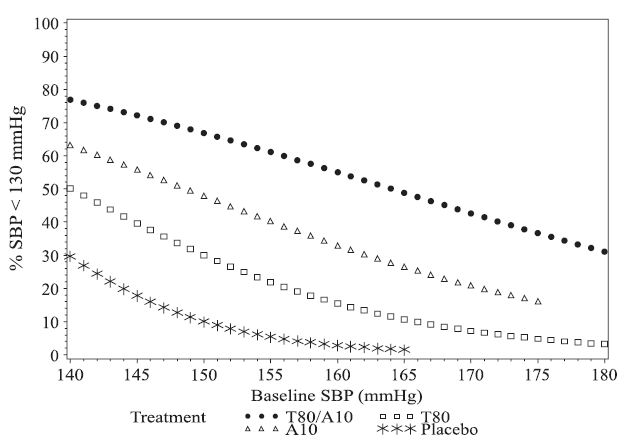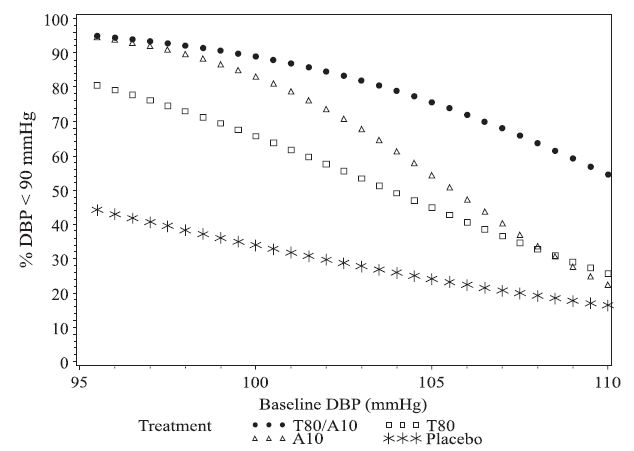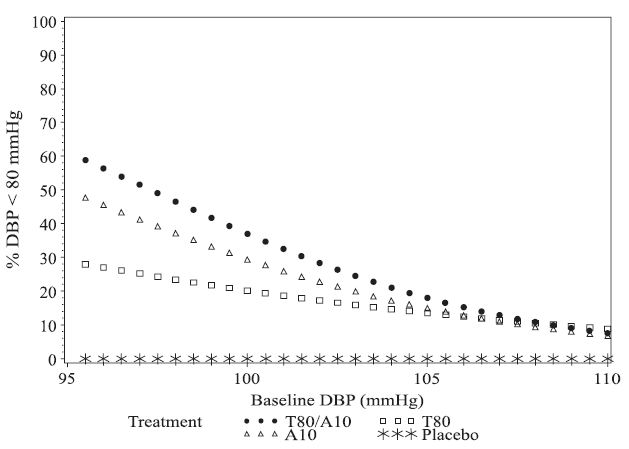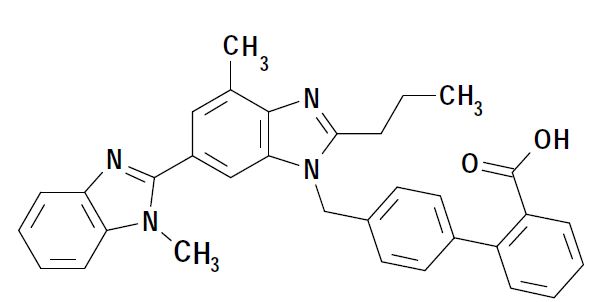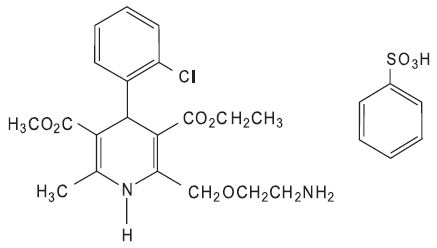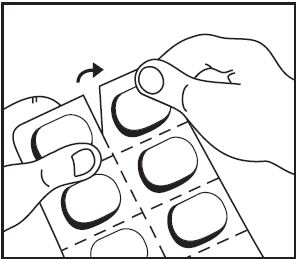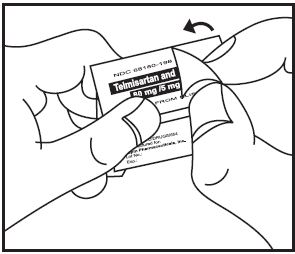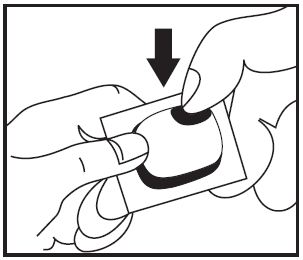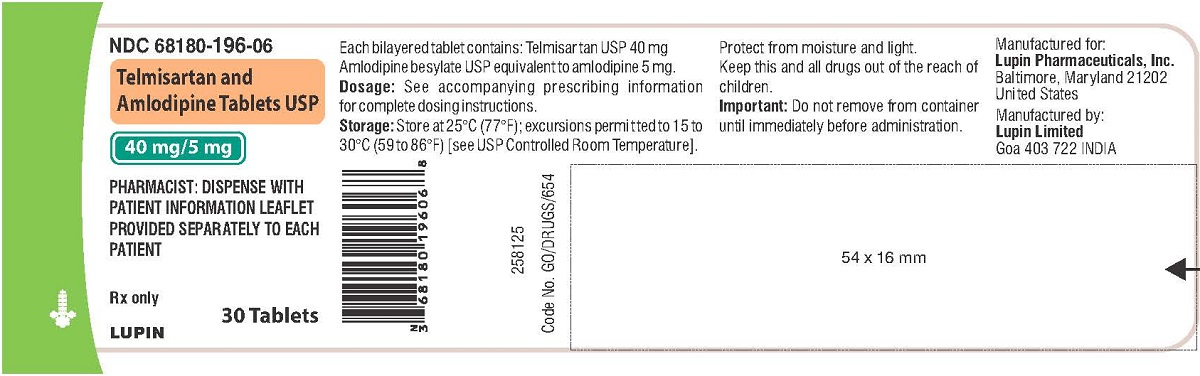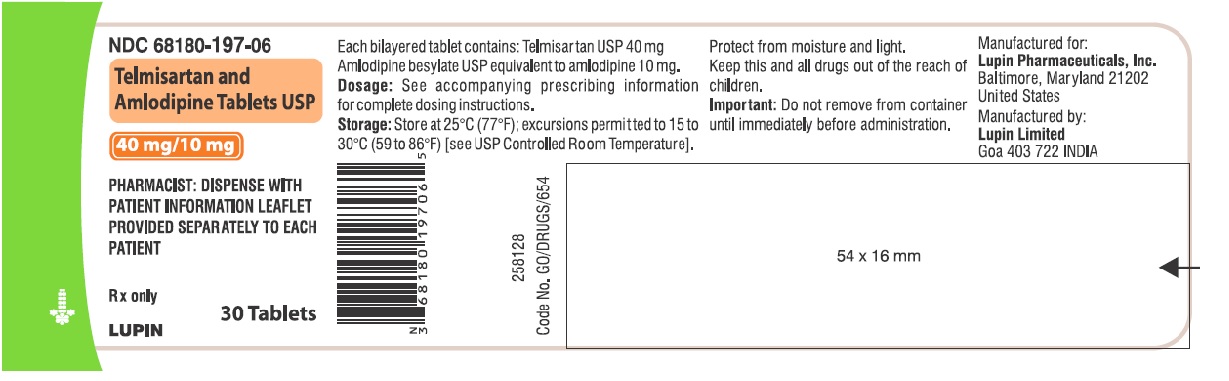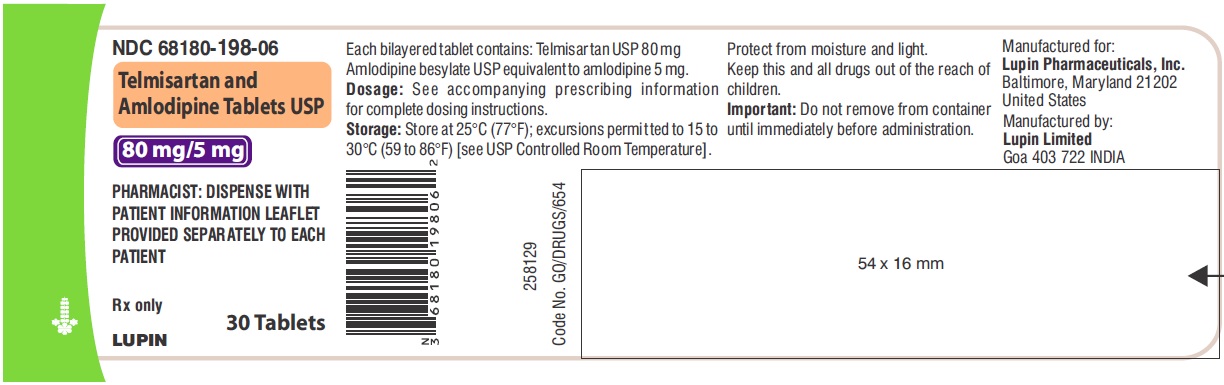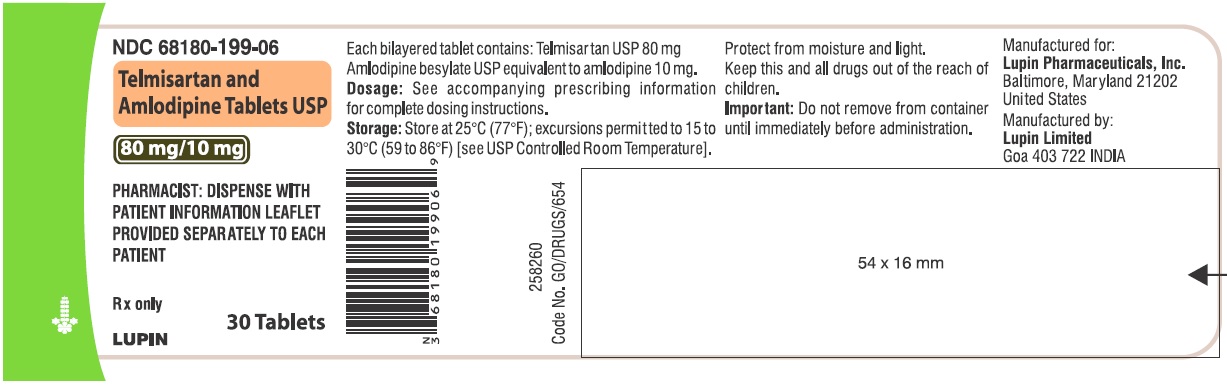 DRUG LABEL: Telmisartan and Amlodipine
NDC: 68180-196 | Form: TABLET
Manufacturer: Lupin Pharmaceuticals, Inc.
Category: prescription | Type: HUMAN PRESCRIPTION DRUG LABEL
Date: 20231215

ACTIVE INGREDIENTS: TELMISARTAN 40 mg/1 1; AMLODIPINE BESYLATE 5 mg/1 1
INACTIVE INGREDIENTS: CROSCARMELLOSE SODIUM; FERRIC OXIDE RED; FERRIC OXIDE YELLOW; MAGNESIUM STEARATE; MANNITOL; POVIDONE; SILICON DIOXIDE; SODIUM HYDROXIDE; SODIUM STARCH GLYCOLATE TYPE A POTATO

HIGHLIGHTS OF PRESCRIBING INFORMATION

These highlights do not include all the information needed to use TELMISARTAN AND AMLODIPINE TABLETS safely and effectively. See full prescribing information for TELMISARTAN AND AMLODIPINE TABLETS.
TELMISARTAN and AMLODIPINE tablets, for oral use
Initial U.S. Approval: 2009

WARNING: FETAL TOXICITY

WARNING: FATAL TOXICITY

See full prescribing information for complete boxed warning.

- When pregnancy is detected, discontinue telmisartan and amlodipine tablets as soon as possible (5.1,8.1)
- Drugs that act directly on the renin-angiotensin system can cause injury and death to the developing fetus (5.1,8.1)

1 INDICATIONS AND USAGE

- Telmisartan and amlodipine tablet is an angiotensin II receptor blocker (ARB) and a dihydropyridine calcium channel blocker (DHP-CCB) combination product indicated for the treatment of hypertension alone or with other antihypertensive agents to lower blood pressure. Lowering blood pressure reduces the risk of fatal and nonfatal cardiovascular events, primarily strokes and myocardial infarctions. (1)
- Telmisartan and amlodipine tablets are indicated as initial therapy in patients likely to need multiple antihypertensive agents to achieve their blood pressure goals (1)

2 DOSAGE AND ADMINISTRATION

- Substitute telmisartan and amlodipine tablets for its individually titrated components for patients on amlodipine and telmisartan. Telmisartan and amlodipine tablets may also be given with increased amounts of amlodipine, telmisartan, or both, as needed. (2.2, 2.3)
- Use telmisartan and amlodipine tablets to provide additional blood pressure lowering for patients not adequately controlled with amlodipine (or another dihydropyridine calcium channel blocker) alone or with telmisartan (or another angiotensin receptor blocker) alone (2.3)
- Dosage may be increased after at least 2 weeks to a maximum dose of 80/10 mg once daily, usually by increasing one component at a time but both components can be raised to achieve more rapid control (2.1, 2.2)
- Majority of antihypertensive effect is attained within 2 weeks (2.1)
- Initiate with 40/5 mg or 80/5 mg once daily (2.4)
- Switch patients who experience dose-limiting adverse reactions on amlodipine to telmisartan and amlodipine tablets containing a lower dose of that component (2.3)

3 DOSAGE FORMS AND STRENGTHS

- Tablets: 40/5 mg, 40/10 mg, 80/5 mg, 80/10 mg (3)

4 CONTRAINDICATIONS

- Known hypersensitivity (e.g., anaphylaxis or angioedema) to telmisartan, amlodipine or any other component of this product (4)
- Do not co-administer aliskiren with telmisartan and amlodipine in patients with diabetes (4)

5 WARNINGS AND PRECAUTIONS

- Avoid fetal or neonatal exposure (5.1)
- Hypotension: Correct any volume or salt depletion before initiating therapy. Observe for signs and symptoms of hypotension. Symptomatic hypotension is possible, particularly in patients with severe aortic stenosis (5.2)
- Titrate slowly in patients with hepatic (5.4) or severe renal impairment (5.5)
- Heart failure: Monitor for worsening (5.8)
- Avoid concomitant use with an ACE inhibitor (5.6)
- Myocardial infarction: Worsening angina and acute myocardial infarction can develop after starting or increasing the dose of telmisartan and amlodipine, particularly in patients with severe obstructive coronary artery disease (5.7)

6 ADVERSE REACTIONS

- In the placebo-controlled factorial design study, the most common reasons for discontinuation of therapy with telmisartan and amlodipine tablets were peripheral edema, dizziness, and hypotension, each leading to discontinuation of ≤0.5% of telmisartan and amlodipine tablets-treated patients. Adverse reactions that occurred at a ≥2% higher incidence on telmisartan and amlodipine tablets than placebo were peripheral edema (4.8% vs 0%), dizziness (3% vs 2.2%), and back pain (2.2% vs 0%). (6.1)

To report SUSPECTED ADVERSE REACTIONS, contact Lupin Pharmaceuticals, Inc. at 1-800-399-2561, or FDA at 1-800-FDA-1088 or www.fda.gov/medwatch.

7 DRUG INTERACTIONS

- NSAIDS: Increased risk of renal impairment and loss of antihypertensive effect (7)
- If simvastatin is co-administered with amlodipine, do not exceed doses greater than 20 mg daily of simvastatin (7)
- Do not co-administer aliskiren with telmisartan and amlodipine in patients with diabetes (7.2)

8 USE IN SPECIFIC POPULATIONS

- Patients ≥75 years of age or hepatically impaired patients: Start with amlodipine or add amlodipine 2.5 mg to telmisartan (2.5, 8.5,8.6)
- Lactation: Do not breastfeed during treatment with telmisartan and amlodipine tablets (8.2)

FULL PRESCRIBING INFORMATION

WARNING: FETAL TOXICITY

- When pregnancy is detected, discontinue telmisartan and amlodipine tablets as soon as possible [see WARNING AND PRECAUTIONS (5.1) and USE IN SPECIFIC POPULATIONS (8.1)].
- Drugs that act directly on the renin-angiotensin system can cause injury and death to the developing fetus [see WARNING AND PRECAUTIONS (5.1) and USE IN SPECIFIC POPULATIONS (8.1)].

1 INDICATIONS AND USAGE

Telmisartan and amlodipine tablets are indicated for the treatment of hypertension, alone or with other antihypertensive agents to lower blood pressure. Lowering blood pressure reduces the risk of fatal and nonfatal cardiovascular events, primarily strokes and myocardial infarctions. These benefits have been seen in controlled trials of antihypertensive drugs from a wide variety of pharmacologic classes including angiotensin II receptor blockers and dihydropyridine calcium channel blockers. There are no controlled trials demonstrating risk reduction with telmisartan and amlodipine tablets.

Control of high blood pressure should be part of comprehensive cardiovascular risk management, including, as appropriate, lipid control, diabetes management, antithrombotic therapy, smoking cessation, exercise, and limited sodium intake. Many patients will require more than one drug to achieve blood pressure goals. For specific advice on goals and management, see published guidelines, such as those of the National High Blood Pressure Education Program's Joint National Committee on Prevention, Detection, Evaluation, and Treatment of High Blood Pressure (JNC).

Numerous antihypertensive drugs, from a variety of pharmacologic classes and with different mechanisms of action, have been shown in randomized controlled trials to reduce cardiovascular morbidity and mortality, and it can be concluded that it is blood pressure reduction, and not some other pharmacologic property of the drugs, that is largely responsible for those benefits. The largest and most consistent cardiovascular outcome benefit has been a reduction in the risk of stroke, but reductions in myocardial infarction and cardiovascular mortality also have been seen regularly.

Elevated systolic or diastolic pressure causes increased cardiovascular risk, and the absolute risk increase per mmHg is greater at higher blood pressures, so that even modest reductions of severe hypertension can provide substantial benefit. Relative risk reduction from blood pressure reduction is similar across populations with varying absolute risk, so the absolute benefit is greater in patients who are at higher risk independent of their hypertension (for example, patients with diabetes or hyperlipidemia), and such patients would be expected to benefit from more aggressive treatment to a lower blood pressure goal.

Some antihypertensive drugs have smaller blood pressure effects (as monotherapy) in black patients, and many antihypertensive drugs have additional approved indications and effects (e.g., on angina, heart failure, or diabetic kidney disease). These considerations may guide selection of therapy.

Telmisartan and amlodipine tablets may also be used as initial therapy in patients who are likely to need multiple drugs to achieve their blood pressure goals.

Base the choice of telmisartan and amlodipine tablets as initial therapy for hypertension on an assessment of potential benefits and risks including whether the patient is likely to tolerate the starting dose of telmisartan and amlodipine tablets.

Patients with moderate or severe hypertension are at relatively high risk for cardiovascular events (such as strokes, heart attacks, and heart failure), kidney failure, and vision problems, so prompt treatment is clinically relevant. Consider the patient's baseline blood pressure, the target goal, and the incremental likelihood of achieving goal with a combination compared with monotherapy when deciding whether to use telmisartan and amlodipine tablets as initial therapy. Individual blood pressure goals may vary based upon the patient's risk.

Data from an 8-week, placebo-controlled, multidose, factorial trial provide estimates of the probability of reaching a blood pressure goal with telmisartan and amlodipine tablets compared to telmisartan or amlodipine monotherapy and placebo [see CLINICAL STUDIES (14.1)].

The figures below provide estimates of the likelihood of achieving systolic and diastolic blood pressure control with telmisartan and amlodipine tablets 80/10 mg, based upon baseline systolic or diastolic blood pressure. The curve of each treatment group was estimated by logistic regression modeling. The estimated likelihood at the right tail of each curve is less reliable due to small numbers of subjects with high baseline blood pressures.

Figure 1a: Probability of Achieving Systolic Blood Pressure <140 mmHg at Week 8
Figure 1b: Probability of Achieving Systolic Blood Pressure <130 mmHg at Week 8
Figure 2a: Probability of Achieving Diastolic Blood Pressure <90 mmHg at Week 8
Figure 2b: Probability of Achieving Diastolic Blood Pressure <80 mmHg at Week 8

The figures above provide an approximation of the likelihood of reaching a targeted blood pressure goal at 8 weeks. For example, a patient with a baseline blood pressure of 160/110 mmHg has about a 16% likelihood of achieving a goal of <140 mmHg (systolic) and 16% likelihood of achieving <90 mmHg (diastolic) on placebo. The likelihood of achieving these same goals on telmisartan is about 46% (systolic) and 26% (diastolic). The likelihood of achieving these same goals on amlodipine is about 69% (systolic) and 22% (diastolic). These likelihoods rise to 79% for systolic and 55% for diastolic with telmisartan and amlodipine tablets.

2 DOSAGE AND ADMINISTRATION

2.1 General Considerations

Telmisartan is an effective treatment of hypertension in once daily doses of 20 to 80 mg while amlodipine is effective in doses of 2.5 to 10 mg.

Dosage must be individualized and may be increased after at least 2 weeks. Most of the antihypertensive effect is apparent within 2 weeks and maximal reduction is generally attained after 4 weeks. The maximum recommended dose of telmisartan and amlodipine tablets is 80/10 mg once daily.

The adverse reactions of telmisartan are uncommon and independent of dose; those of amlodipine are a mixture of dose-dependent phenomena (primarily peripheral edema) and dose-independent phenomena, the former much more common than the latter [see ADVERSE REACTIONS (6.1)].

Telmisartan and amlodipine tablets may be taken with or without food.

2.2 Replacement Therapy

Patients receiving amlodipine and telmisartan from separate tablets may instead receive telmisartan and amlodipine tablets containing the same component doses once daily. When substituting for individual components, increase the dose of telmisartan and amlodipine tablets if blood pressure control has not been satisfactory.

2.3 Add-on Therapy for Patients with Hypertension Not Adequately Controlled on Antihypertensive Monotherapy

Telmisartan and amlodipine tablets may be used to provide additional blood pressure lowering for patients not adequately controlled with amlodipine (or another dihydropyridine calcium channel blocker) alone or with telmisartan (or another angiotensin receptor blocker) alone.

Patients treated with 10 mg amlodipine who experience any dose-limiting adverse reactions such as edema, may be switched to telmisartan and amlodipine tablets 40/5 mg once daily, reducing the dose of amlodipine without reducing the overall expected antihypertensive response [see ADVERSE REACTIONS (6.1)].

2.4 Initial Therapy

A patient may be initiated on telmisartan and amlodipine tablets if it is unlikely that control of blood pressure would be achieved with a single agent. The usual starting dose of telmisartan and amlodipine tablet is 40/5 mg once daily. Patients requiring larger blood pressure reductions may be started on telmisartan and amlodipine tablet 80/5 mg once daily.

Initial therapy with telmisartan and amlodipine tablet is not recommended in patients ≥75 years old or with hepatic impairment [see DOSAGE AND ADMINISTRATION (2.5), WARNINGS AND PRECAUTIONS (5.4), and USE IN SPECIFIC POPULATIONS (8.5,8.6)].

Correct imbalances of intravascular volume- or salt-depletion, before initiating therapy with telmisartan and amlodipine tablets [see WARNINGS AND PRECAUTIONS (5.2)].

2.5 Dosing in Specific Populations

Renal Impairment

No initial dosage adjustment is required for patients with mild or moderate renal impairment. Titrate slowly in patients with severe renal impairment.

Hepatic Impairment

In most patients, initiate amlodipine therapy at 2.5 mg. Titrate slowly in patients with hepatic impairment.

Patients 75 Years of Age and Older

In most patients, initiate amlodipine therapy at 2.5 mg. Titrate slowly in patients 75 years of age and older.

3 DOSAGE FORMS AND STRENGTHS

Telmisartan and amlodipine tablets USP are formulated for oral administration in the following strength combinations:

40 mg/5 mg

Oval shaped, biconvex, bilayer, uncoated tablets where Amlodipine layer is white but may have yellow specks, debossed with 'C54' and Telmisartan layer is yellow in colour but may have white specks, debossed with 'LU'.

40 mg/10 mg

Oval shaped, biconvex, bilayer, uncoated tablets where Amlodipine layer is white but may have red specks, debossed with 'C55' and Telmisartan layer is red in colour but may have white specks, debossed with 'LU'.

80 mg/5 mg

Capsule shaped, biconvex, bilayer, uncoated tablets where Amlodipine layer is white but may have red specks, debossed with 'C56' and Telmisartan layer is red in colour but may have white specks, debossed with 'LU'.

80 mg/10 mg

Capsule shaped, biconvex, bilayer, uncoated tablet where Amlodipine layer is white but may have yellow specks, debossed with 'C57' and Telmisartan layer is yellow in colour but may have white specks, debossed with 'LU'.

4 CONTRAINDICATIONS

Telmisartan and amlodipine tablets are contraindicated in patients with known hypersensitivity (e.g., anaphylaxis or angioedema) to telmisartan, amlodipine, or any other component of this product [see ADVERSE REACTIONS (6.2)].

Do not co-administer aliskiren with telmisartan and amlodipine tablets in patients with diabetes [see DRUG INTERACTIONS (7.2)].

5 WARNINGS AND PRECAUTIONS

5.1 Fetal Toxicity

Use of drugs that act on the renin-angiotensin system during the second and third trimesters of pregnancy reduces fetal renal function and increases fetal and neonatal morbidity and death. Resulting oligohydramnios can be associated with fetal lung hypoplasia and skeletal deformations. Potential neonatal adverse effects include skull hypoplasia, anuria, hypotension, renal failure, and death. When pregnancy is detected, discontinue telmisartan and amlodipine tablets as soon as possible [see USE IN SPECIFIC POPULATIONS (8.1)].

5.2 Hypotension

Telmisartan

In patients with an activated renin-angiotensin system, such as volume- or salt-depleted patients (e.g., those being treated with high doses of diuretics), symptomatic hypotension may occur after initiation of therapy with telmisartan and amlodipine tablets. Either correct this condition prior to administration of telmisartan and amlodipine tablets, or start treatment under close medical supervision with a reduced dose.

If hypotension does occur, place the patient in the supine position and, if necessary, give an intravenous infusion of normal saline. A transient hypotensive response is not a contraindication to further treatment, which usually can be continued without difficulty once the blood pressure has stabilized.

Amlodipine

Symptomatic hypotension is possible, particularly in patients with severe aortic stenosis. Because of the gradual onset of action, acute hypotension is unlikely.

5.3 Hyperkalemia

Telmisartan

Hyperkalemia may occur in patients on ARBs, particularly in patients with advanced renal impairment, heart failure, on renal replacement therapy, or on potassium supplements, potassium-sparing diuretics, potassium-containing salt substitutes or other drugs that increase potassium levels. Consider periodic determinations of serum electrolytes to detect possible electrolyte imbalances, particularly in patients at risk.

5.4 Patients with Impaired Hepatic Function

Telmisartan

As the majority of telmisartan is eliminated by biliary excretion, patients with biliary obstructive disorders or hepatic insufficiency can be expected to have reduced clearance. Initiate telmisartan at low doses and titrate slowly in these patients [see DOSAGE AND ADMINISTRATION (2.5), USE IN SPECIFIC POPULATIONS (8.6), and CLINICAL PHARMACOLOGY (12.3)].

Amlodipine

Amlodipine is extensively metabolized by the liver and the plasma elimination half-life (t1/2) is 56 hours in patients with impaired hepatic function. Since patients with hepatic impairment have decreased clearance of amlodipine, start amlodipine or add amlodipine at 2.5 mg in patients with hepatic impairment. The lowest dose of telmisartan and amlodipine tablet is 40/5 mg; therefore, initial therapy with telmisartan and amlodipine tablet is not recommended in hepatically impaired patients [see USE IN SPECIFIC POPULATIONS (8.6)].

5.5 Renal Function Impairment

Telmisartan

As a consequence of inhibiting the renin-angiotensin-aldosterone system, anticipate changes in renal function in susceptible individuals. In patients whose renal function may depend on the activity of the renin-angiotensin-aldosterone system (e.g., patients with severe congestive heart failure or renal dysfunction), treatment with angiotensin-converting enzyme (ACE) inhibitors and angiotensin receptor antagonists has been associated with oliguria and/or progressive azotemia and (rarely) with acute renal failure and/or death. Similar results may be anticipated in patients treated with telmisartan [see CLINICAL PHARMACOLOGY (12.3)].

In studies of ACE inhibitors in patients with unilateral or bilateral renal artery stenosis, increases in serum creatinine or blood urea nitrogen were observed. There has been no long term use of telmisartan in patients with unilateral or bilateral renal artery stenosis, but anticipate an effect similar to that seen with ACE inhibitors.

5.6 Dual Blockade of the Renin-Angiotensin-Aldosterone System (RAS)

Telmisartan

Dual blockade of the RAS with angiotensin-receptor blockers, ACE inhibitors, or aliskiren is associated with increased risks of hypotension, hyperkalemia, and changes in renal function (including acute renal failure) compared to monotherapy.

The ONTARGET trial enrolled 25,620 patients ≥55 years old with atherosclerotic disease or diabetes with end-organ damage, randomized them to telmisartan only, ramipril only, or the combination, and followed them for a median of 56 months. Patients receiving the combination of telmisartan and ramipril did not obtain any additional benefit compared to monotherapy, but experienced an increased incidence of renal dysfunction (e.g., acute renal failure) compared with groups receiving telmisartan alone or ramipril alone.

In most patients no benefit has been associated with using two RAS inhibitors concomitantly. In general, avoid combined use of RAS inhibitors. Closely monitor blood pressure, renal function and electrolytes in patients on telmisartan and amlodipine and other agents that affect the RAS.

Do not co-administer aliskiren with telmisartan and amlodipine in patients with diabetes. Avoid concomitant use of aliskiren with telmisartan and amlodipine in patients with renal impairment (GFR <60 mL/min /1.73 m^2).

5.7 Risk of Myocardial Infarction or Increased Angina

Amlodipine

Worsening angina and acute myocardial infarction can develop after starting or increasing the dose of telmisartan and amlodipine tablets, particularly in patients with severe obstructive coronary artery disease.

5.8 Heart Failure

Amlodipine

Closely monitor patients with heart failure.

Amlodipine (5 to10 mg per day) has been studied in a placebo-controlled trial of 1153 patients with NYHA Class III or IV heart failure on stable doses of ACE inhibitor, digoxin, and diuretics. Follow-up was at least 6 months, with a mean of about 14 months. There was no overall adverse effect on survival or cardiac morbidity (as defined by life-threatening arrhythmia, acute myocardial infarction, or hospitalization for worsened heart failure). Amlodipine has been compared to placebo in four 8 to12 week studies of patients with NYHA class II/III heart failure, involving a total of 697 patients. In these studies, there was no evidence of worsening of heart failure based on measures of exercise tolerance, NYHA classification, symptoms, or LVEF. In the PRAISE-2 study, 1654 patients with NYHA class III (80%) or IV (20%) heart failure without evidence of underlying ischemic disease, on stable doses of ACE inhibitor (99%), digitalis (99%), and diuretics (99%) were randomized 1:1 to receive placebo or amlodipine and followed for a mean of 33 months. While there was no statistically significant difference between amlodipine and placebo in the primary endpoint of all cause mortality (95% confidence limits from 8% reduction to 29% increase on amlodipine), there were more reports of pulmonary edema in the patients on amlodipine.

6 ADVERSE REACTIONS

6.1 Clinical Trials Experience

Because clinical studies are conducted under widely varying conditions, adverse reactions rates observed in the clinical studies of a drug cannot be directly compared to rates in the clinical studies of another drug and may not reflect the rates observed in practice.

Telmisartan and Amlodipine Tablets

The concomitant use of telmisartan and amlodipine has been evaluated for safety in more than 3700 patients with hypertension; approximately 1900 of these patients were exposed for at least 6 months and over 160 of these patients were exposed for at least one year. Adverse reactions have generally been mild and transient in nature and have only infrequently required discontinuation of therapy.

In the placebo-controlled factorial design study, the population treated with a telmisartan and amlodipine combination had a mean age of 53 years and included approximately 50% males, 79% were Caucasian, 17% Blacks, and 4% Asians. Patients received doses ranging from 20/2.5 mg to 80/10 mg orally, once daily.

The frequency of adverse reactions was not related to gender, age, or race.

The adverse reactions that occurred in the placebo-controlled factorial design trial in ≥2% of patients treated with telmisartan and amlodipine and at a higher incidence in telmisartan and amlodipine-treated patients (n=789) than placebo-treated patients (n=46) were peripheral edema (4.8% vs 0%), dizziness (3% vs 2.2%), and back pain (2.2% vs 0%). Edema (other than peripheral edema), hypotension, and syncope were reported in <2% of patients treated with telmisartan and amlodipine tablets.

In the placebo-controlled factorial design trial, discontinuation due to adverse events occurred in 2.2% of all treatment cells of patients in the telmisartan/amlodipine-treated patients and in 4.3% in the placebo-treated group. The most common reasons for discontinuation of therapy with telmisartan and amlodipine tablets were peripheral edema, dizziness, and hypotension (each ≤0.5%).

Peripheral edema is a known, dose-dependent adverse reaction of amlodipine, but not of telmisartan. In the factorial design study, the incidence of peripheral edema during the 8 week, randomized, double-blind treatment period was highest with amlodipine 10 mg monotherapy. The incidence was notably lower when telmisartan was used in combination with amlodipine 10 mg.

Table 1: Incidence of Peripheral Edema During the 8 Week Treatment Period
 |  | Telmisartan
 |  | Placebo | 40 mg | 80 mg
Amlodipine | Placebo 5 mg 10 mg | 0% 0.7% 17.8% | 0.8% 1.4% 6.2% | 0.7% 2.1% 11.3%

Telmisartan

Telmisartan has been evaluated for safety in more than 3700 patients, including 1900 treated for over 6 months and more than 1300 for over one year. Adverse experiences have generally been mild and transient in nature and have only infrequently required discontinuation of therapy.

In placebo-controlled trials involving 1041 patients treated with various doses of telmisartan (20 to 160 mg) monotherapy for up to 12 weeks, an overall incidence of adverse events was similar to the patients treated with placebo.

Adverse events occurring at an incidence of ≥1% in patients treated with telmisartan and at a greater rate than in patients treated with placebo, irrespective of their causal association, are presented in Table 2.

Table 2: Adverse Events Occurring at an Incidence of ≥1% in Patients Treated with Telmisartan and at a Greater Rate than Patients Treated with Placebo
 | Telmisartan n=1455 % | Placebo n=380 %
Upper respiratory tract infection | 7 | 6
Back pain | 3 | 1
Sinusitis | 3 | 2
Diarrhea | 3 | 2
Pharyngitis | 1 | 0

In addition to the adverse events in the table, the following events occurred at a rate of ≥1% but were at least as frequent in the placebo group: influenza-like symptoms, dyspepsia, myalgia, urinary tract infection, abdominal pain, headache, dizziness, pain, fatigue, coughing, hypertension, chest pain, nausea, and peripheral edema. Discontinuation of therapy because of adverse events was required in 2.8% of 1455 patients treated with telmisartan tablets and 6.1% of 380 placebo patients in placebo-controlled clinical trials.

The incidence of adverse events was not dose-related and did not correlate with gender, age, or race of patients.

The incidence of cough occurring with telmisartan in 6 placebo-controlled trials was identical to that noted for placebo-treated patients (1.6%).

In addition to those listed above, adverse events that occurred in >0.3% of 3500 patients treated with telmisartan monotherapy in controlled or open trials are listed below. It cannot be determined whether these events were causally related to telmisartan tablets:

Autonomic Nervous System:

Impotence, increased sweating, flushing

Body as a Whole:

Allergy, fever, leg pain, malaise

Cardiovascular:

Palpitation, dependent edema, angina pectoris, tachycardia, leg edema, abnormal ECG

CNS:

Insomnia, somnolence, migraine, vertigo, paresthesia, involuntary muscle contractions, hypoesthesia

Gastrointestinal:

Flatulence, constipation, gastritis, vomiting, dry mouth, hemorrhoids, gastroenteritis, enteritis, gastroesophageal reflux, toothache, non specific gastrointestinal disorders

Metabolic:

Gout, hypercholesterolemia, diabetes mellitus

Musculoskeletal:

Arthritis, arthralgia, leg cramps

Psychiatric:

Anxiety, depression, nervousness

Resistance Mechanism:

Infection, fungal infection, abscess, otitis media

Respiratory:

Asthma, bronchitis, rhinitis, dyspnea, epistaxis

Skin:

Dermatitis, rash, eczema, pruritus

Urinary:

Micturition frequency, cystitis

Vascular:

Cerebrovascular disorder

Special Senses:

Abnormal vision, conjunctivitis, tinnitus, earache.

During initial clinical studies, a single case of angioedema was reported (among a total of 3781 patients treated).

Clinical Laboratory Findings:

In placebo-controlled clinical trials, clinically relevant changes in standard laboratory test parameters were rarely associated with administration of telmisartan tablets.

Hemoglobin

A greater than 2 g/dL decrease in hemoglobin was observed in 0.8% telmisartan patients compared with 0.3% placebo patients. No patients discontinued therapy due to anemia.

Creatinine

A 0.5 mg/dL rise or greater in creatinine was observed in 0.4% telmisartan patients compared with 0.3% placebo patients. One telmisartan-treated patient discontinued therapy due to increases in creatinine and blood urea nitrogen.

Liver Enzymes

Occasional elevations of liver chemistries occurred in patients treated with telmisartan; all marked elevations occurred at a higher frequency with placebo. No telmisartan-treated patients discontinued therapy due to abnormal hepatic function.

Amlodipine

Amlodipine has been evaluated for safety in more than 11,000 patients in U.S. and foreign clinical trials. Most adverse reactions reported during therapy with amlodipine were of mild or moderate severity. In controlled clinical trials directly comparing amlodipine (n=1730) in doses up to 10 mg to placebo (n=1250), discontinuation of amlodipine due to adverse reactions was required in only about 1.5% of amlodipine-treated patients and was not significantly different from that seen in placebo-treated patients (about 1%). The most common side effects were headache and edema. The incidence (%) of side effects which occurred in a dose-related manner are presented in Table 3.

Table 3: Incidence (%) of Dose-Related Adverse Effects with Amlodipine at Doses of 2.5 mg, 5.0 mg, and 10.0 mg or Placebo
Header Adverse Event | Amlodipine 2.5 mg n=275 % | Amlodipine 5.0 mg n=296 % | Amlodipine 10.0 mg n=268 % | Placebo n=520 %
Edema | 1.8 | 3.0 | 10.8 | 0.6
Dizziness | 1.1 | 3.4 | 3.4 | 1.5
Flushing | 0.7 | 1.4 | 2.6 | 0.0
Palpitations | 0.7 | 1.4 | 4.5 | 0.6

Other adverse experiences which were not clearly dose related but which were reported with an incidence greater than 1% in placebo-controlled clinical trials are presented in Table 4.

Table 4: Incidence (%) of Adverse Effects Not Clearly Dose Related but Reported at an Incidence of >1% in Placebo-Controlled Clinical Trials
Adverse Event | Amlodipine n=1730 % | Placebo n=1250 %
Headache | 7.3 | 7.8
Fatigue | 4.5 | 2.8
Nausea | 2.9 | 1.9
Abdominal pain | 1.6 | 0.3
Somnolence | 1.4 | 0.6

The following events occurred in <1% but >0.1% of patients in controlled clinical trials or under conditions of open trials or marketing experience where a causal relationship is uncertain; they are listed to alert the physician to a possible relationship:

Cardiovascular:

Arrhythmia (including ventricular tachycardia and atrial fibrillation), bradycardia, chest pain, hypotension, peripheral ischemia, syncope, tachycardia, postural dizziness, postural hypotension, vasculitis

Central and Peripheral Nervous System:

Hypoesthesia, neuropathy peripheral, paresthesia, tremor, vertigo

Gastrointestinal:

Anorexia, constipation, dyspepsia,** dysphagia, diarrhea, flatulence, pancreatitis, vomiting, gingival hyperplasia, change of bowel habit

General:

Allergic reaction, asthenia,** back pain, hot flushes, malaise, pain, rigors, weight gain, weight decrease

Musculoskeletal System:

Arthralgia, arthrosis, muscle cramps,** myalgia

Psychiatric:

Sexual dysfunction (male** and female), insomnia, nervousness, depression, abnormal dreams, anxiety, depersonalization, mood change

Respiratory System:

Dyspnea,** epistaxis

Skin and Appendages:

Angioedema, erythema multiforme, pruritus,** rash,** rash erythematous, rash maculopapular

Special Senses:

Abnormal vision, conjunctivitis, diplopia, eye pain, tinnitus

Urinary System:

Micturition frequency, micturition disorder, nocturia

Autonomic Nervous System:

Dry mouth, sweating increased

Metabolic and Nutritional:

Hyperglycemia, thirst

Hemopoietic:

Leukopenia, purpura, thrombocytopenia.

**These events occurred in less than 1% in placebo-controlled trials, but the incidence of these side effects was between 1% and 2% in all multiple dose studies.

The following events occurred in <0.1% of patients: cardiac failure, pulse irregularity, extrasystoles, skin discoloration, urticaria, skin dryness, alopecia, dermatitis, muscle weakness, twitching, ataxia, hypertonia, migraine, cold and clammy skin, apathy, agitation, amnesia, gastritis, increased appetite, loose stools, coughing, rhinitis, dysuria, polyuria, parosmia, taste perversion, abnormal visual accommodation, and xerophthalmia.

Other reactions occurred sporadically and cannot be distinguished from medications or concurrent disease states such as myocardial infarction and angina.

Amlodipine has not been associated with clinically significant changes in routine laboratory tests. No clinically relevant changes were noted in serum potassium, serum glucose, total triglycerides, total cholesterol, HDL cholesterol, uric acid, blood urea nitrogen, or creatinine.

Amlodipine has been used safely in patients with chronic obstructive pulmonary disease, well-compensated congestive heart failure, coronary artery disease, peripheral vascular disease, diabetes mellitus, and abnormal lipid profiles.

Adverse reactions reported for amlodipine for indications other than hypertension may be found in the prescribing information for Norvasc®.

6.2 Postmarketing Experience

The following adverse reactions have been identified during post-approval use of telmisartan or amlodipine. Because these reactions are reported voluntarily from a population of uncertain size, it is not always possible to estimate reliably their frequency or establish a causal relationship to drug exposure. Decisions to include these reactions in labeling are typically based on one or more of the following factors: (1) seriousness of the reaction, (2) frequency of reporting, or (3) strength of causal connection to telmisartan or amlodipine.

Telmisartan

The most frequently spontaneously reported events include: headache, dizziness, asthenia, coughing, nausea, fatigue, weakness, edema, face edema, lower limb edema, angioneurotic edema, urticaria, hypersensitivity, sweating increased, erythema, chest pain, atrial fibrillation, congestive heart failure, myocardial infarction, blood pressure increased, hypertension aggravated, hypotension (including postural hypotension), hyperkalemia, syncope, dyspepsia, diarrhea, pain, urinary tract infection, erectile dysfunction, back pain, abdominal pain, muscle cramps (including leg cramps), myalgia, bradycardia, eosinophilia, thrombocytopenia, uric acid increased, abnormal hepatic function/liver disorder, renal impairment including acute renal failure, anemia, and increased CPK, anaphylactic reaction, tendon pain (including tendonitis, tenosynovitis), drug eruption (e.g. toxic skin eruption mostly reported as toxicoderma, rash, and urticaria), hypoglycemia (in diabetic patients), and angioedema (with fatal outcome).

Rare cases of rhabdomyolysis have been reported in patients receiving angiotensin II receptor blockers, including telmisartan.

Amlodipine

Gynecomastia has been reported infrequently and a causal relationship is uncertain. Jaundice and hepatic enzyme elevations (mostly consistent with cholestasis or hepatitis), in some cases severe enough to require hospitalization, have been reported in association with use of amlodipine.

Postmarketing reporting has also revealed a possible association between extrapyramidal disorder and amlodipine.

7 DRUG INTERACTIONS

7.1 Drug Interactions with Telmisartan and Amlodipine Tablets

The pharmacokinetics of amlodipine and telmisartan are not altered when the drugs are co-administered.

No drug interaction studies have been conducted with telmisartan and amlodipine tablets and other drugs, although studies have been conducted with the individual amlodipine and telmisartan components of telmisartan and amlodipine tablets, as described below:

7.2 Drug Interactions with Telmisartan

Aliskiren

Do not co-administer aliskiren with telmisartan and amlodipine tablets in patients with diabetes. Avoid use of aliskiren with telmisartan and amlodipine tablets in patients with renal impairment (GFR <60 mL/min).

Digoxin

When telmisartan was co-administered with digoxin, median increases in digoxin peak plasma concentration (49%) and in trough concentration (20%) were observed. Therefore, monitor digoxin levels when initiating, adjusting, and discontinuing telmisartan for the purpose of keeping the digoxin level within the therapeutic range.

Lithium

Reversible increases in serum lithium concentrations and toxicity have been reported during concomitant administration of lithium with angiotensin II receptor antagonists including telmisartan. Therefore, monitor serum lithium levels during concomitant use.

Non-Steroidal Anti-Inflammatory Agents including Selective Cyclooxygenase-2 Inhibitors (COX-2 Inhibitors)

In patients who are elderly, volume-depleted (including those on diuretic therapy), or with compromised renal function, co-administration of NSAIDs, including selective COX-2 inhibitors, with angiotensin II receptor antagonists, including telmisartan, may result in deterioration of renal function, including possible acute renal failure. These effects are usually reversible. Monitor renal function periodically in patients receiving telmisartan and NSAID therapy.

The antihypertensive effect of angiotensin II receptor antagonists, including telmisartan may be attenuated by NSAIDs including selective COX-2 inhibitors.

7.3 Drug Interactions with Amlodipine

In clinical trials, amlodipine has been safely administered with thiazide diuretics, beta-blockers, angiotensin-converting enzyme inhibitors, long-acting nitrates, sublingual nitroglycerin, digoxin, warfarin, non-steroidal anti-inflammatory drugs, antibiotics, and oral hypoglycemic drugs.

Simvastatin

Co-administration of multiple doses of 10 mg of amlodipine with 80 mg simvastatin resulted in a 77% increase in exposure to simvastatin compared to simvastatin alone. Limit the dose of simvastatin in patients on amlodipine to 20 mg daily.

Immunosuppressants

Amlodipine may increase the systemic exposure of cyclosporine or tacrolimus when co-administered. Frequent monitoring of trough blood levels of cyclosporin and tacrolimus and dose adjustment when appropriate is recommended.

The following have no clinically relevant effects on the pharmacokinetics of amlodipine: cimetidine, grapefruit juice, magnesium and aluminum hydroxide antacid, sildenafil.

Amlodipine has no clinically relevant effects on the pharmacokinetics or pharmacodynamics of the following: atorvastatin, digoxin, warfarin.

CYP3A4 Inhibitors

Co-administration of a 180 mg daily dose of diltiazem with 5 mg amlodipine in elderly hypertensive patients resulted in a 60% increase in amlodipine systemic exposure. Erythromycin co-administration in healthy volunteers did not significantly change amlodipine systemic exposure. However, strong inhibitors of CYP3A4 (e.g., ketoconazole, itraconazole, ritonavir) may increase the plasma concentrations of amlodipine to a greater extent. Monitor for symptoms of hypotension and edema when amlodipine is co-administered with CYP3A4 inhibitors.

CYP3A4 Inducers

No information is available on the quantitative effects of CYP3A4 inducers (e.g., carbamazepine, phenobarbital, phenytoin, fosphenytoin, primidone, rifampicin, St. John's Wort) on amlodipine. Patients should be monitored for adequate clinical effect when amlodipine is co-administered with CYP3A4 inducers.

8 USE IN SPECIFIC POPULATIONS

8.1 Pregnancy

Risk Summary

Telmisartan and amlodipine tablets can cause fetal harm when administered to a pregnant woman. Use of drugs that act on the renin-angiotensin system during the second and third trimesters of pregnancy reduces fetal renal function and increases fetal and neonatal morbidity and death (see Clinical Considerations). Most epidemiologic studies examining fetal abnormalities after exposure to antihypertensive use in the first trimester have not distinguished drugs affecting the renin-angiotensin system from other antihypertensive agents. Studies in rats and rabbits with telmisartan showed fetotoxicity only at maternally toxic doses (see Data). In animal reproduction studies, there was no evidence of adverse developmental effects when pregnant rats and rabbits were treated orally with amlodipine maleate during organogenesis at doses approximately 10 and 20-times the maximum recommended human dose (MRHD), respectively. However for rats, litter size was significantly decreased (by about 50%) and the number of intrauterine deaths was significantly increased (about 5-fold). Amlodipine has been shown to prolong both the gestation period and the duration of labor in rats at this dose (see Data). When pregnancy is detected, discontinue telmisartan and amlodipine tablets as soon as possible.

The estimated background risk of major birth defects and miscarriage for the indicated population is unknown. All pregnancies have a background risk of birth defect, loss, or other adverse outcomes. In the U.S. general population, the estimated background risk of major malformations and miscarriage in clinically recognized pregnancies is 2% to 4%, and 15% to 20%, respectively.

Clinical Considerations

Disease-associated maternal and/or embryo/fetal risk:

Hypertension in pregnancy increases the maternal risk for pre-eclampsia, gestational diabetes, premature delivery, and delivery complications (e.g., need for cesarean section, and post-partum hemorrhage). Hypertension increases the fetal risk for intrauterine growth restriction and intrauterine death. Pregnant women with hypertension should be carefully monitored and managed accordingly.

Fetal/Neonatal adverse reactions:

Use of drugs that act on the RAS in the second and third trimesters of pregnancy can result in the following: oligohydramnios, reduced fetal renal function leading to anuria and renal failure, fetal lung hypoplasia, skeletal deformations, including skull hypoplasia, hypotension, and death. In the unusual case that there is no appropriate alternative to therapy with drugs affecting the renin-angiotensin system for a particular patient, apprise the mother of the potential risk to the fetus.

In patients taking telmisartan and amlodipine tablets during pregnancy, perform serial ultrasound examinations to assess the intra-amniotic environment. Fetal testing may be appropriate, based on the week of gestation. If oligohydramnios is observed, discontinue telmisartan and amlodipine tablets, unless it is considered lifesaving for the mother. Patients and physicians should be aware, however, that oligohydramnios may not appear until after the fetus has sustained irreversible injury.

Closely observe infants with histories of in utero exposure to telmisartan and amlodipine tablets for hypotension, oliguria, and hyperkalemia. If oliguria or hypotension occurs, support blood pressure and renal perfusion. Exchange transfusions or dialysis may be required as a means of reversing hypotension and/or substituting for disordered renal function [see USE IN SPECIFIC POPULATIONS (8.4)].

Data

Animal Data:

No reproductive toxicity studies have been conducted with the combination of telmisartan and amlodipine besylate. However, these studies have been conducted for telmisartan and amlodipine besylate alone.

Telmisartan:

No teratogenic effects were observed when telmisartan was administered to pregnant rats at oral doses of up to 50 mg/kg/day and to pregnant rabbits at oral doses up to 45 mg/kg/day. In rabbits, embryolethality associated with maternal toxicity (reduced body weight gain and food consumption) was observed at 45 mg/kg/day [about 12 times the maximum recommended human dose (MRHD) of 80 mg on a mg/m^2 basis]. In rats, maternally toxic (reduction in body weight gain and food consumption) telmisartan doses of 15 mg/kg/day (about 1.9 times the MRHD on a mg/m^2 basis), administered during late gestation and lactation, were observed to produce adverse effects in neonates, including reduced viability, low birth weight, delayed maturation, and decreased weight gain. The no observed effect doses for developmental toxicity in rats and rabbits, 5 and 15 mg/kg/day, respectively, are about 0.64 and 3.7 times, on a mg/m^2 basis, the maximum recommended human dose of telmisartan (80 mg/day).

Amlodipine:

No evidence of teratogenicity or embryo/fetal toxicity was found when pregnant rats and rabbits were treated orally with amlodipine maleate at doses up to 10 mg amlodipine/kg/day (approximately 10 and 20 times the MRHD based on body surface area, respectively) during their respective periods of major organogenesis. However, for rats, litter size was significantly decreased (by about 50%) and the number of intrauterine deaths was significantly increased (about 5-fold). Amlodipine has been shown to prolong both the gestation period and the duration of labor in rats at this dose.

8.2 Lactation

Risk Summary

There is no information regarding the presence of telmisartan and amlodipine tablets or telmisartan in human milk, the effects on the breastfed infant, or the effects on milk production. Limited published studies report that amlodipine is present in human milk. However, there is insufficient information to determine the effects of amlodipine on the breastfed infant. There is no available information on the effects of amlodipine on milk production. Telmisartan is present in the milk of lactating rats (see Data). Because of the potential for serious adverse reactions in the breastfed infant including hypotension, hyperkalemia and renal impairment, advise a nursing woman not to breastfeed during treatment with telmisartan and amlodipine tablets.

Data:

Telmisartan was present in the milk of lactating rats at concentrations 1.5 to 2 times those found in plasma from 4 to 8 hours after administration.

8.4 Pediatric Use

Safety and effectiveness of telmisartan and amlodipine tablets in pediatric patients have not been established.

Neonates with a history of in utero exposure to telmisartan and amlodipine

If oliguria or hypotension occurs, support blood pressure and renal perfusion. Exchange transfusions or dialysis may be required as a means of reversing hypotension and/or substituting for disordered renal function.

8.5 Geriatric Use

Telmisartan and Amlodipine Tablets

Of the total number of 3282 hypertensive patients receiving a telmisartan/amlodipine combination in clinical studies, 605 (18%) patients were 65 years of age or older and of these, 88 (3%) patients were 75 years and older. No overall differences in efficacy or safety of telmisartan and amlodipine tablets were observed in this patient population.

Telmisartan

Of the total number of patients receiving telmisartan in clinical studies, 551 (18.6%) were 65 to 74 years of age and 130 (4.4%) were 75 years and older. No overall differences in effectiveness and safety were observed in these patients compared to younger patients and other reported clinical experience has not identified differences in responses between the elderly and younger patients, but greater sensitivity of some older individuals cannot be ruled out.

Amlodipine

Clinical studies of amlodipine besylate tablets did not include sufficient numbers of subjects aged 65 and over to determine whether they respond differently from younger subjects. Other reported clinical experience has not identified differences in responses between the elderly and younger patients. In general, dose selection for an elderly patient should be cautious, usually starting at the low end of the dosing range, reflecting the greater frequency of decreased hepatic, renal or cardiac function, and of concomitant disease or other drug therapy. Elderly patients have decreased clearance of amlodipine with a resulting increase of AUC of approximately 40% to 60%, and a lower initial dose may be required. Since patients age 75 and older have decreased clearance of amlodipine, start amlodipine or add amlodipine 2.5 mg to telmisartan. The lowest dose of telmisartan and amlodipine tablet is 40/5 mg; therefore, initial therapy with telmisartan and amlodipine tablets is not recommended in patients 75 years of age and older [see DOSAGE AND ADMINISTRATION (2.5)].

8.6 Hepatic Insufficiency

Monitor carefully and uptitrate slowly in patients with biliary obstructive disorders or hepatic insufficiency [see DOSAGE AND ADMINISTRATION (2) and WARNINGS AND PRECAUTIONS (5.4)]. Since patients with hepatic impairment have decreased clearance of amlodipine, start amlodipine or add amlodipine 2.5 mg to telmisartan. The lowest dose of telmisartan and amlodipine tablet is 40/5 mg; therefore, initial therapy with telmisartan and amlodipine tablet is not recommended in hepatically impaired patients [see DOSAGE AND ADMINISTRATION (2.4)].

8.7 Race

The magnitude of blood pressure lowering in black patients approached that observed in non-black patients but the number of black patients was limited (237 of 1461 patients).

10 OVERDOSAGE

Telmisartan

Limited data are available with regard to overdosage in humans. The most likely manifestations of overdosage with telmisartan tablets would be hypotension, dizziness, and tachycardia; bradycardia could occur from parasympathetic (vagal) stimulation. If symptomatic hypotension should occur, supportive treatment should be instituted. Telmisartan is not removed by hemodialysis.

Amlodipine

Overdosage might be expected to cause excessive peripheral vasodilation with marked hypotension and possibly a reflex tachycardia. In humans, experience with intentional overdosage of amlodipine is limited.

Single oral doses of amlodipine maleate equivalent to 40 mg amlodipine/kg and 100 mg amlodipine/kg in mice and rats, respectively, caused deaths. Single oral amlodipine maleate doses equivalent to 4 or more mg amlodipine/kg or higher in dogs (11 or more times the maximum recommended human dose on a mg/m^2 basis) caused a marked peripheral vasodilation and hypotension.

If massive overdose should occur, initiate active cardiac and respiratory monitoring. Frequent blood pressure measurements are essential. Should hypotension occur, provide cardiovascular support including elevation of the extremities and the judicious administration of fluids. If hypotension remains unresponsive to these conservative measures, consider administration of vasopressors (such as phenylephrine) with attention to circulating volume and urine output. As amlodipine is highly protein bound, hemodialysis is not likely to be of benefit.

11 DESCRIPTION

Telmisartan and amlodipine tablet USP is a fixed dose combination of telmisartan and amlodipine.

Telmisartan and amlodipine tablets USP contain telmisartan, a non-peptide angiotensin II receptor (type AT1) antagonist. Telmisartan is a white to slightly yellowish solid. It is practically insoluble in water and in the pH range of 3 to 9, sparingly soluble in strong acid (except insoluble in hydrochloric acid), and soluble in strong base. Telmisartan is chemically described as 4'-[(1,4'-dimethyl-2'-propyl [2,6'-bi-1H-benzimidazol]-1'-yl)methyl]-[1,1'-biphenyl]-2-carboxylic acid. Its empirical formula is C33H30N4O2 and its structural formula is:

Telmisartan and amlodipine tablets USP contain the besylate salt of amlodipine, a dihydropyridine calcium-channel blocker (CCB). Amlodipine besylate is a white to pale yellow crystalline powder, slightly soluble in water and sparingly soluble in ethanol. Amlodipine besylate's chemical name is 3-Ethyl-5-methyl(4RS)-2-[(2-aminoethoxy)methyl]-4-(2-chlorophenyl)-6-methyl-1,4-dihydropyridine-3,5-dicarboxylate benzenesulphonate. Its empirical formula is C20H25ClN2O5•C6H6O3S and its structural formula is:

Telmisartan and amlodipine tablets USP are formulated in four strengths for oral administration with a combination of amlodipine besylate, equivalent to 5 mg or 10 mg of amlodipine free-base, with 40 mg, or 80 mg of telmisartan provided in the following four combinations: 40/5 mg, 40/10 mg, 80/5 mg, and 80/10 mg.

Telmisartan and amlodipine tablets USP also contain the following inactive ingredients: colloidal silicon dioxide, crosscarmellose sodium, ferric oxide red, ferric oxide yellow, mannitol, magnesium stearate, povidone, sodium hydroxide and sodium starch glycolate.

Telmisartan and amlodipine tablets USP are hygroscopic and require protection from moisture.

Telmisartan and amlodipine tablets USP require protection from light.

12 CLINICAL PHARMACOLOGY

12.1 Mechanism of Action

Telmisartan

Angiotensin II is formed from angiotensin I in a reaction catalyzed by angiotensin-converting enzyme (ACE, kininase II). Angiotensin II is the principal pressor agent of the renin-angiotensin system, with effects that include vasoconstriction, stimulation of synthesis and release of aldosterone, cardiac stimulation, and renal reabsorption of sodium. Telmisartan blocks the vasoconstrictor and aldosterone-secreting effects of angiotensin II by selectively blocking the binding of angiotensin II to the AT1 receptor in many tissues, such as vascular smooth muscle and the adrenal gland. Its action is therefore independent of the pathways for angiotensin II synthesis.

There is also an AT2 receptor found in many tissues, but AT2 is not known to be associated with cardiovascular homeostasis. Telmisartan has much greater affinity (>3,000 fold) for the AT1 receptor than for the AT2 receptor.

Blockade of the renin-angiotensin system with ACE inhibitors, which inhibit the biosynthesis of angiotensin II from angiotensin I, is widely used in the treatment of hypertension. ACE inhibitors also inhibit the degradation of bradykinin, a reaction also catalyzed by ACE. Because telmisartan does not inhibit ACE (kininase II), it does not affect the response to bradykinin. Whether this difference has clinical relevance is not yet known. Telmisartan does not bind to or block other hormone receptors or ion channels known to be important in cardiovascular regulation.

Blockade of the angiotensin II receptor inhibits the negative regulatory feedback of angiotensin II on renin secretion, but the resulting increased plasma renin activity and angiotensin II circulating levels do not overcome the effect of telmisartan on blood pressure.

Amlodipine

Amlodipine is a dihydropyridine calcium channel blocker that inhibits the transmembrane influx of calcium ions into vascular smooth muscle and cardiac muscle. Experimental data suggest that amlodipine binds to both dihydropyridine and nondihydropyridine binding sites. The contractile processes of cardiac muscle and vascular smooth muscle are dependent upon the movement of extracellular calcium ions into these cells through specific ion channels. Amlodipine inhibits calcium ion influx across cell membranes selectively, with a greater effect on vascular smooth muscle cells than on cardiac muscle cells. Negative inotropic effects can be detected in vitro but such effects have not been seen in intact animals at therapeutic doses. Serum calcium concentration is not affected by amlodipine. Within the physiologic pH range, amlodipine is an ionized compound (pKa=8.6), and its kinetic interaction with the calcium channel receptor is characterized by a gradual rate of association and dissociation with the receptor binding site, resulting in a gradual onset of effect.

Amlodipine is a peripheral arterial vasodilator that acts directly on vascular smooth muscle to cause a reduction in peripheral vascular resistance and reduction in blood pressure.

12.2 Pharmacodynamics

Telmisartan and Amlodipine Tablets

Telmisartan and amlodipine tablets have been shown to be effective in lowering blood pressure. Telmisartan and amlodipine tablet is a combination of two drugs with antihypertensive properties: a dihydropyridine calcium antagonist (calcium ion antagonist or slow-channel blocker), amlodipine besylate, and an angiotensin II receptor blocker, telmisartan.

Both telmisartan and amlodipine lower blood pressure by reducing peripheral resistance but through complementary mechanisms.

Telmisartan

In normal volunteers, a dose of telmisartan 80 mg inhibited the pressor response to an intravenous infusion of angiotensin II by about 90% at peak plasma concentrations with approximately 40% inhibition persisting for 24 hours.

Plasma concentration of angiotensin II and plasma renin activity (PRA) increased in a dose-dependent manner after single administration of telmisartan to healthy subjects and repeated administration to hypertensive patients. The once-daily administration of up to 80 mg telmisartan to healthy subjects did not influence plasma aldosterone concentrations. In multiple dose studies with hypertensive patients, there were no clinically significant changes in electrolytes (serum potassium or sodium), or in metabolic function (including serum levels of cholesterol, triglycerides, HDL, LDL, glucose, or uric acid).

In 30 hypertensive patients with normal renal function treated for 8 weeks with telmisartan 80 mg or telmisartan 80 mg in combination with hydrochlorothiazide 12.5 mg, there were no clinically significant changes from baseline in renal blood flow, glomerular filtration rate, filtration fraction, renovascular resistance, or creatinine clearance.

Telmisartan has indications other than hypertension which can be found in the Micardis® (telmisartan) tablets package insert.

Amlodipine

Following administration of therapeutic doses to patients with hypertension, amlodipine produces vasodilation resulting in a reduction of supine and standing blood pressures. These decreases in blood pressure are not accompanied by a significant change in heart rate or plasma catecholamine levels with chronic dosing. Although the acute intravenous administration of amlodipine decreases arterial blood pressure and increases heart rate in hemodynamic studies of patients with chronic stable angina, chronic oral administration of amlodipine in clinical trials did not lead to clinically significant changes in heart rate or blood pressures in normotensive patients with angina.

With chronic once daily administration, antihypertensive effectiveness is maintained for at least 24 hours. Plasma concentrations correlate with effect in both young and elderly patients. The magnitude of reduction in blood pressure with amlodipine is also correlated with the height of pretreatment elevation; thus, individuals with moderate hypertension (diastolic pressure 105 to 114 mmHg) had about a 50% greater response than patients with mild hypertension (diastolic pressure 90 to 104 mmHg). Normotensive subjects experienced no clinically significant change in blood pressure (+1/-2 mmHg).

In hypertensive patients with normal renal function, therapeutic doses of amlodipine resulted in a decrease in renal vascular resistance and an increase in glomerular filtration rate and effective renal plasma flow without change in filtration fraction or proteinuria.

As with other calcium channel blockers, hemodynamic measurements of cardiac function at rest and during exercise (or pacing) in patients with normal ventricular function treated with amlodipine have generally demonstrated a small increase in cardiac index without significant influence on dP/dt or on left ventricular end diastolic pressure or volume. In hemodynamic studies, amlodipine has not been associated with a negative inotropic effect when administered in the therapeutic dose range to intact animals and man, even when co-administered with beta-blockers to man. Similar findings, however, have been observed in normal or well-compensated patients with heart failure with agents possessing significant negative inotropic effects.

Amlodipine does not change sinoatrial nodal function or atrioventricular conduction in intact animals or man. In patients with chronic stable angina, intravenous administration of 10 mg did not significantly alter A-H and H-V conduction and sinus node recovery time after pacing. Similar results were obtained in patients receiving amlodipine and concomitant beta-blockers. In clinical studies in which amlodipine was administered in combination with beta-blockers to patients with either hypertension or angina, no adverse effects of electrocardiographic parameters were observed. In clinical trials with angina patients alone, amlodipine therapy did not alter electrocardiographic intervals or produce higher degrees of AV blocks.

Amlodipine has indications other than hypertension which can be found in the Norvasc® package insert.

12.3 Pharmacokinetics

Telmisartan and Amlodipine Tablets

The pharmacokinetics of amlodipine and telmisartan when combined are similar to the pharmacokinetics of amlodipine and telmisartan when administered separately.

After administering telmisartan and amlodipine tablets 80/10 mg with a high-fat meal, the total area under the plasma concentration-time curve (AUC) and Cmax for telmisartan decreased by about 24% and 60%, respectively. For amlodipine, AUC and Cmax were not altered [see DOSAGE AND ADMINISTRATION (2.1)].

Telmisartan

Following oral administration, peak concentrations (Cmax) of telmisartan are reached in 0.5 to 1 hour after dosing. Food slightly reduces the bioavailability of telmisartan, with a reduction in the area under the plasma concentration-time curve (AUC) of about 6% with the 40 mg tablet and about 20% after a 160 mg dose. The absolute bioavailability of telmisartan is dose dependent. At 40 and 160 mg the bioavailability was 42% and 58%, respectively. The pharmacokinetics of orally administered telmisartan are nonlinear over the dose range 20 to 160 mg, with greater than proportional increases of plasma concentrations (Cmax and AUC) with increasing doses. Telmisartan shows bi-exponential decay kinetics with a terminal elimination half life of approximately 24 hours. Trough plasma concentrations of telmisartan with once daily dosing are about 10% to 25% of peak plasma concentrations. Telmisartan has an accumulation index in plasma of 1.5 to 2.0 upon repeated once daily dosing.

Amlodipine

Peak plasma concentrations of amlodipine are reached 6 to 12 hours after administration of amlodipine alone. Absolute bioavailability has been estimated to be between 64% and 90%. The bioavailability of amlodipine is not altered by the presence of food.

Elimination of amlodipine from the plasma is biphasic with a terminal elimination half-life of about 30 to 50 hours. Steady state plasma levels of amlodipine are reached after 7 to 8 days of consecutive daily dosing.

Distribution

Telmisartan:

Telmisartan is highly bound to plasma proteins (>99.5%), mainly albumin and α1 - acid glycoprotein. Plasma protein binding is constant over the concentration range achieved with recommended doses. The volume of distribution for telmisartan is approximately 500 liters indicating additional tissue binding.

Amlodipine:

The apparent volume of distribution of amlodipine is 21 L/kg. Approximately 93% of circulating amlodipine is bound to plasma proteins in hypertensive patients.

Metabolism and Elimination

Telmisartan:

Following either intravenous or oral administration of ^14C-labeled telmisartan, most of the administered dose (>97%) was eliminated unchanged in feces via biliary excretion; only minute amounts were found in the urine (0.91% and 0.49% of total radioactivity, respectively).

Telmisartan is metabolized by conjugation to form a pharmacologically inactive acylglucuronide; the glucuronide of the parent compound is the only metabolite that has been identified in human plasma and urine. After a single dose, the glucuronide represents approximately 11% of the measured radioactivity in plasma. The cytochrome P450 isoenzymes are not involved in the metabolism of telmisartan.

Total plasma clearance of telmisartan is >800 mL/min. Terminal half-life and total clearance appear to be independent of dose.

Amlodipine:

Amlodipine is extensively (about 90%) converted to inactive metabolites via hepatic metabolism with 10% of the parent compound and 60% of the metabolites excreted in the urine.

Specific Populations

Renal Insufficiency:

Telmisartan

No dosage adjustment is necessary in patients with decreased renal function. Telmisartan is not removed from blood by hemofiltration [see WARNINGS AND PRECAUTIONS (5.5)].

Amlodipine

The pharmacokinetics of amlodipine are not significantly influenced by renal impairment. Patients with renal failure may therefore receive the usual initial dose.

Hepatic Insufficiency:

Telmisartan

In patients with hepatic insufficiency, plasma concentrations of telmisartan are increased, and absolute bioavailability approaches 100% [see WARNINGS AND PRECAUTIONS (5.4) and USE IN SPECIFIC POPULATIONS (8.6)].

Amlodipine

Patients with hepatic insufficiency have decreased clearance of amlodipine with a resulting increase in AUC of approximately 40% to 60%. Therefore, start with a low initial dose of amlodipine.

Gender:

Plasma concentrations of telmisartan are generally 2 to 3 times higher in females than in males. In clinical trials, however, no significant increases in blood pressure response or in the incidence of orthostatic hypotension were found in women. No dosage adjustment is necessary.

Geriatric Patients:

Telmisartan

The pharmacokinetics of telmisartan do not differ between the elderly and those younger than 65 years [see DOSAGE AND ADMINISTRATION (2.1)].

Amlodipine

Elderly patients have decreased clearance of amlodipine with a resulting increase in AUC of approximately 40% to 60%. Therefore, start with a low initial dose of amlodipine [see DOSAGE AND ADMINISTRATION (2.5)].

Drug Interaction Studies

Telmisartan:

Ramipril and Ramiprilat

Co-administration of telmisartan 80 mg once daily and ramipril 10 mg once daily to healthy subjects increases steady-state Cmax and AUC of ramipril 2.3-and 2.1-fold, respectively, and Cmax and AUC of ramiprilat 2.4-and 1.5-fold, respectively. In contrast, Cmax and AUC of telmisartan decrease by 31% and 16%, respectively. When co-administering telmisartan and ramipril, the response may be greater because of the possibly additive pharmacodynamic effects of the combined drugs, and also because of the increased exposure to ramipril and ramiprilat in the presence of telmisartan.

Other Drugs

Co-administration of telmisartan did not result in a clinically significant interaction with acetaminophen, amlodipine, glyburide, simvastatin, hydrochlorothiazide, warfarin, or ibuprofen. Telmisartan is not metabolized by the cytochrome P450 system and had no effects in vitro on cytochrome P450 enzymes, except for some inhibition of CYP2C19. Telmisartan is not expected to interact with drugs that inhibit cytochrome P450 enzymes; it is also not expected to interact with drugs metabolized by cytochrome P450 enzymes, except for possible inhibition of the metabolism of drugs metabolized by CYP2C19.

13 NONCLINICAL TOXICOLOGY

13.1 Carcinogenesis, Mutagenesis, Impairment of Fertility

Telmisartan

There was no evidence of carcinogenicity when telmisartan was administered in the diet to mice and rats for up to 2 years. The highest doses administered to mice (1000 mg/kg/day) and rats (100 mg/kg/day) are, on a mg/m^2 basis, about 59 and 13 times, respectively, the maximum recommended human dose (MRHD) of telmisartan. These same doses have been shown to provide average systemic exposures to telmisartan >100 times and >25 times, respectively, the systemic exposure in humans receiving the MRHD (80 mg/day).

Genotoxicity assays did not reveal any telmisartan-related effects at either the gene or chromosome level. These assays included bacterial mutagenicity tests with Salmonella and E. coli (Ames), a gene mutation test with Chinese hamster V79 cells, a cytogenetic test with human lymphocytes, and a mouse micronucleus test.

No drug-related effects on the reproductive performance of male and female rats were noted at 100 mg/kg/day (the highest dose administered), about 13 times, on a mg/m^2 basis, the MRHD of telmisartan. This dose in the rat resulted in an average systemic exposure (telmisartan AUC as determined on day 6 of pregnancy) at least 50 times the average systemic exposure in humans at the MRHD (80 mg/day).

Amlodipine

Rats and mice treated with amlodipine maleate in the diet for up to two years, at concentrations calculated to provide daily dosage levels of 0.5, 1.25, and 2.5 mg amlodipine/kg/day, showed no evidence of a carcinogenic effect of the drug. For the mouse, the highest dose was, on mg/m^2 basis, similar to the maximum recommended human dose [MRHD] of 10 mg amlodipine/day. For the rat, the highest dose was, on a mg/m^2 basis, about two and a half times the MRHD. (Calculations based on a 60 kg patient.)

Mutagenicity studies conducted with amlodipine maleate revealed no drug-related effects at either the gene or chromosome level.

There was no effect on the fertility of rats treated orally with amlodipine maleate (males for 64 days and females for 14 days prior to mating) at doses of up to 10 mg amlodipine/kg/day (about 10 times the MRHD of 10 mg/day on a mg/m^2 basis).

14 CLINICAL STUDIES

14.1 Telmisartan and Amlodipine Tablets

The efficacy of telmisartan and amlodipine tablets for treatment of hypertension was studied in 1 placebo-controlled and 2 active-controlled trials.

An 8-week multicenter, randomized, double-blind, placebo-controlled, parallel group factorial study in patients with mild to severe hypertension was conducted to determine if treatment with telmisartan and amlodipine tablet was more effective in reducing blood pressure compared to the respective monotherapies. The study randomized 1461 patients with baseline systolic blood pressure between 117 and 179 mmHg (mean 153 mmHg) and a baseline diastolic blood pressure between 90 and 119 (mean 102 mmHg) to one of the 16 treatment arms. Patients assigned to receive amlodipine 10 mg started on amlodipine 5 mg or combinations thereof for the first two weeks. The four key treatment combinations (including combinations of telmisartan 40 or 80 mg and amlodipine 5 or 10 mg) had statistically significant reduction in in-clinic seated trough cuff systolic and diastolic blood pressure compared to the respective individual monotherapies (Table 5).

Table 5: Placebo-Subtracted Mean Change from Baseline in Seated Systolic/Diastolic Blood Pressure (mmHg): Combination Therapy vs Monotherapy Components
Header$ Amlodipine, mg | Telmisartan, mg
 | 0 | 40 | 80
0 | — | -12.1/-7.2 | -11.8/-7.8
5 | -12.9/-7.2 | -19.3/-10.3 | -19.6/-12.0
10 | -18.2/-10.9 | -22.2/-14.0 | -23.9/-13.9

The majority of the antihypertensive effect of the telmisartan/amlodipine combination was attained within 2 weeks after initiation of therapy. In patients receiving a telmisartan/amlodipine combination significantly larger reductions in seated diastolic and systolic blood pressure compared to patients treated with the respective monotherapies were observed at every assessment (Week 2, 4, 6, and 8).

The antihypertensive effect of telmisartan and amlodipine tablets was similar in patients ≥65 years than below 65 years of age, in male and female patients, and in patients with and without diabetes.

The magnitude of blood pressure lowering in black patients approached that observed in non-black patients but the number of black patients was limited (237 of 1461 patients).

Automated ambulatory blood pressure monitoring (ABPM) performed in a subset of 562 patients confirmed the results seen with in-clinic systolic and diastolic blood pressure reductions over the entire 24-hour dosing period.

In a double-blind, active-controlled study, a total of 1097 patients with mild to severe hypertension (mean baseline systolic/diastolic BP 149.5/96.6 mmHg) who were not adequately controlled on amlodipine 5 mg received telmisartan and amlodipine (40/5 mg or 80/5 mg) or amlodipine alone (5 mg or 10 mg). After 8 weeks administration, each of the combination treatments was statistically significantly superior to both amlodipine monotherapy doses in reducing diastolic and systolic blood pressures. Edema related events (peripheral edema, generalized edema, and edema) in patients who received telmisartan and amlodipine (40/5 mg or 80/5 mg) were significantly lower as compared to patients who received amlodipine 10 mg (4.3% vs 27.2%, respectively).

Table 6: Effect on Seated Systolic/Diastolic Blood Pressure: Combination Therapy vs Monotherapy
Header$ Treatment Group | Mean Change^2 | Difference from amlodipine 5 mg | Difference from amlodipine 10 mg
Telmisartan and amlodipine 40/5 mg; n=270 | -13.6 / -9.4 | -7.4^1/ - 3.6^1 | -2.4^1 / -1.4^1
Telmisartan and amlodipine 80/5 mg; n=271 | -15.0 / -10.6 | -8.8^1 / -4.9^1 | -3.9^1 / -2.7^1
Amlodipine 5 mg; n=255 | -6.2 / -5.7 | ---- | ----
Amlodipine 10 mg; n=261 | -11.1 / -8.0 | ---- | ----
^1p<0.05
^2Mean change from baseline at Week 8 in seated systolic/diastolic blood pressure

In a second double-blind, active-controlled study, a total of 947 patients with mild to severe hypertension (mean baseline systolic/diastolic BP 147.5/95.6 mmHg) who were not adequately controlled on amlodipine 10 mg received telmisartan and amlodipine (40/10 mg or 80/10 mg) or amlodipine alone (10 mg). After 8 weeks, each of the combination treatments was statistically significantly superior to amlodipine monotherapy in reducing diastolic and systolic blood pressures.

Table 7: Effect on Seated Systolic/Diastolic Blood Pressure: Combination Therapy vs Monotherapy
Treatment Group | Mean Change [Mean change from baseline at Week 8 in seated systolic/diastolic blood pressure] | Difference from amlodipine 10 mg
Telmisartan and amlodipine 40/10 mg; n=306 | -11.1 / -9.2 | -3.7 [p<0.05] / -2.8
Telmisartan and amlodipine 80/10 mg; n=310 | -11.3 / -9.3 | -3.9 / -2.8
Amlodipine 10 mg; n=305 | -7.4 / -6.5 | ----

There are no trials of telmisartan and amlodipine demonstrating reductions in cardiovascular risk in patients with hypertension, but at least one pharmacologically similar drug has demonstrated such benefits.

14.2 Telmisartan

The antihypertensive effects of telmisartan have been demonstrated in six principal placebo-controlled clinical trials, studying a range of 20 to 160 mg; one of these examined the antihypertensive effects of telmisartan and hydrochlorothiazide in combination. The studies involved a total of 1773 patients with mild to moderate hypertension (diastolic blood pressure of 95 to 114 mmHg), 1031 of whom were treated with telmisartan. Following once daily administration of telmisartan, the magnitude of blood pressure reduction from baseline after placebo subtraction was approximately (SBP/DBP) 6 to 8/6 mmHg for 20 mg, 9 to 13/6 to 8 mmHg for 40 mg, and 12 to 13/7 to 8 mmHg for 80 mg. Larger doses (up to 160 mg) did not appear to cause a further decrease in blood pressure.

Upon initiation of antihypertensive treatment with telmisartan, blood pressure was reduced after the first dose, with a maximal reduction by about 4 weeks. With cessation of treatment with telmisartan tablets, blood pressure gradually returned to baseline values over a period of several days to one week. During long term studies (without placebo control) the effect of telmisartan appeared to be maintained for up to at least one year. The antihypertensive effect of telmisartan is not influenced by patient age, gender, weight, or body mass index. Blood pressure response in black patients (usually a low-renin population) is noticeably less than that in Caucasian patients. This has been true for most, but not all, angiotensin II antagonists and ACE inhibitors.

In a controlled study, the addition of telmisartan to hydrochlorothiazide produced an additional dose-related reduction in blood pressure that was similar in magnitude to the reduction achieved with telmisartan monotherapy. Hydrochlorothiazide also had an added blood pressure effect when added to telmisartan.

The onset of antihypertensive activity occurs within 3 hours after administration of a single oral dose. At doses of 20, 40, and 80 mg, the antihypertensive effect of once daily administration of telmisartan is maintained for the full 24-hour dose interval. With automated ambulatory blood pressure monitoring and conventional blood pressure measurements, the 24-hour trough-to-peak ratio for 40 to 80 mg doses of telmisartan was 70% to 100% for both systolic and diastolic blood pressure. The incidence of symptomatic orthostasis after the first dose in all controlled trials was low (0.04%).

There were no changes in the heart rate of patients treated with telmisartan in controlled trials.

14.3 Amlodipine

The antihypertensive efficacy of amlodipine has been demonstrated in a total of 15 double-blind, placebo-controlled, randomized studies involving 800 patients on amlodipine and 538 on placebo. Once daily administration produced statistically significant placebo-corrected reductions in supine and standing blood pressures at 24 hours post-dose, averaging about 12/6 mmHg in the standing position and 13/7 mmHg in the supine position in patients with mild to moderate hypertension. Maintenance of the blood pressure effect over the 24-hour dosing interval was observed, with little difference in peak and trough effect.

16 HOW SUPPLIED/STORAGE AND HANDLING

Telmisartan and amlodipine tablets USP are available as

40 mg/5 mg

Oval shaped, biconvex, bilayer, uncoated tablets where Amlodipine layer is white but may have yellow specks, debossed with 'C54' and Telmisartan layer is yellow in colour but may have white specks, debossed with 'LU'.

40 mg/10 mg

Oval shaped, biconvex, bilayer, uncoated tablets where Amlodipine layer is white but may have red specks, debossed with 'C55' and Telmisartan layer is red in colour but may have white specks, debossed with 'LU'.

80 mg/5 mg

Capsule shaped, biconvex, bilayer, uncoated tablets where Amlodipine layer is white but may have red specks, debossed with 'C56' and Telmisartan layer is red in colour but may have white specks, debossed with 'LU'.

80 mg/10 mg

Capsule shaped, biconvex, bilayer, uncoated tablet where Amlodipine layer is white but may have yellow specks, debossed with 'C57' and Telmisartan layer is yellow in colour but may have white specks, debossed with 'LU'.

Telmisartan and amlodipine tablets USP are supplied for oral administration in the following strengths and package configurations:

Tablet strength (telmisartan/ amlodipine besylate equivalent to amlodipine) mg | Package Configuration | NDC#
40 mg/5 mg | Bottles of 30 Bottles of 90 A box containing 100 Tablets (10 X 10 unit-dose) | 68180-196-06 68180-196-09 68180-196-13
40 mg/10 mg | Bottles of 30 Bottles of 90 A box containing 100 Tablets (10 X 10 unit-dose) | 68180-197-06 68180-197-09 68180-197-13
80 mg/5 mg | Bottles of 30 Bottles of 90 A box containing 100 Tablets (10 X 10 unit-dose) | 68180-198-06 68180-198-09 68180-198-13
80 mg/10 mg | Bottles of 30 Bottles of 90 A box containing 100 Tablets (10 X 10 unit-dose) | 68180-199-06 68180-199-09 68180-199-13

Storage

Store at 25°C (77°F); excursions permitted to 15 to 30°C (59 to 86°F) [see USP Controlled Room Temperature].

Do not remove from blisters until immediately before administration. Protect from moisture and light.

17 PATIENT COUNSELING INFORMATION

Advise the patient to read the FDA-approved patient labeling (Patient Information).

Pregnancy

Advise female patients of childbearing age about the consequences of exposure to telmisartan and amlodipine tablets during pregnancy. Discuss treatment options with women planning to become pregnant. Tell patients should be asked to report pregnancies to their physicians as soon as possible [see WARNINGS AND PRECAUTIONS (5.1) and USE IN SPECIFIC POPULATIONS (8.1)].

Lactation

Advise nursing women not to breastfeed during treatment with telmisartan and amlodipine tablets [see USE IN SPECIFIC POPULATIONS (8.2)].

Symptomatic Hypotension

Advise patients that lightheadedness can occur, especially during the first days of therapy, and to report it to their healthcare provider. Inform patients that inadequate.fluid intake, excessive perspiration, diarrhea, or vomiting can lead to an excessive fall in blood pressure, with the same consequences of lightheadedness and possible.syncope. Advise patients to contact their healthcare provider if syncope occurs [see WARNINGS AND PRECAUTIONS (5.2)].

® The brands listed are trademarks of their respective owners and are not trademarks of Lupin Pharmaceuticals, Inc. The makers of these brands are not affiliated with and do not endorse Lupin Pharmaceuticals, Inc. or its products.

Manufactured for:

Lupin Pharmaceuticals, Inc.

Baltimore, Maryland 21202

United States

Manufactured by:

Lupin Limited

Goa 403 722 INDIA

Revised: April 2019 ID#: 258261

Patient Information

Telmisartan and Amlodipine Tablets,

(TEL-mi-SAR-tan And am-LOE-di-peen)

40 mg/5 mg, 40 mg/ 10 mg, 80 mg/5 mg and 80 mg /10 mg

Rx only

Read this Patient Information before you start taking telmisartan and amlodipine tablets and each time you get a refill. There may be new information. This information does not take the place of talking to your doctor about your medical condition or your treatment.

What is the most important information I should know about Telmisartan and Amlodipine Tablets?

Telmisartan and amlodipine tablets can cause harm or death to an unborn baby. Talk to your doctor about other ways to lower your blood pressure if you plan to become pregnant. If you get pregnant while taking telmisartan and amlodipine tablets, tell your doctor right away.

What is Telmisartan and Amlodipine Tablet?

Telmisartan and amlodipine tablet is a prescription medicine that contains telmisartan and amlodipine. Telmisartan and amlodipine tablets may be used to treat high blood pressure (hypertension):

- when one of these medicines (or a similar one) is not enough to lower your high blood pressure
- as the first medicine to lower your high blood pressure if your doctor decides you are likely to need more than one medicine

It is not known if telmisartan and amlodipine tablets are safe and effective in children.

Who should not take Telmisartan and Amlodipine Tablets?

You should not take telmisartan and amlodipine tablets if you are allergic (hypersensitive) to the active ingredients (telmisartan or amlodipine) or any of the other ingredients listed at the end of this leaflet.

For patients with diabetes, if you are taking telmisartan and amlodipine tablets you should not take aliskiren.

What should I tell my doctor before taking Telmisartan and Amlodipine Tablets?

Before you take telmisartan and amlodipine tablets, tell your doctor if you:

- are pregnant or are planning to become pregnant. See "What is the most important information I should know about Telmisartan and Amlodipine Tablets ?"
- are breast-feeding or plan to breast-feed. Telmisartan and amlodipine tablets can pass into your breast milk and may harm your baby. You and your doctor should decide if you will take telmisartan and amlodipine tablets or breast-feed. You should not do both. Talk with your doctor about the best way to feed your baby if you take telmisartan and amlodipine tablets.
- have liver problems
- have kidney problems
- have heart problems
- have any other medical conditions

Tell your doctor about all the medicines you take, including prescription and nonprescription medicines, vitamins and herbal supplements.

For patients with diabetes, if you are taking telmisartan and amlodipine tablets you should not take aliskiren.

Telmisartan and amlodipine tablets may affect the way other medicines work, and other medicines may affect how telmisartan and amlodipine tablets works. Especially tell your doctor if you take:

- aliskiren
- digoxin (Lanoxin®)
- lithium (Lithobid®, lithium carbonate, lithium citrate)
- aspirin or other non-steroidal anti-inflammatory drugs (NSAIDs)
- other medicines that may be used to treat high blood pressure or a heart problem
- simvastatin (Zocor®, Vytorin®)
- water pills (diuretics)

Know the medicines you take. Keep a list of them and show it to your doctor or pharmacist when you get a new medicine.

How should I take Telmisartan and Amlodipine Tablets?

- Take telmisartan and amlodipine tablets exactly as your doctor tells you to take it.
- Your doctor will tell you how much telmisartan and amlodipine tablets to take and when to take it. Your doctor may change your dose if needed.
- Take telmisartan and amlodipine tablets one time each day at the same time.
- Take telmisartan and amlodipine tablets with or without food.
- If you miss a dose, take it as soon as you remember. If it is close to your next dose, do not take the missed dose. Take the next dose at your regular time.
- If you take too much telmisartan and amlodipine tablets, call your doctor or go to the nearest hospital emergency room right away.
- Read the "How to Open the Blister " at the end of this leaflet before you use telmisartan and amlodipine tablets. Talk with your doctor if you do not understand the instructions.

What are possible side effects of Telmisartan and Amlodipine Tablets?

Telmisartan and amlodipine tablets may cause serious side effects, including:

- Injury or death to your unborn baby. See "What is the most important information I should know about telmisartan and amlodipine tablets? "
- Low blood pressure (hypotension) is most likely to happen if you also:

• take water pills (diuretics)

• are on a low-salt diet

• get dialysis treatments

• have heart problems

• get sick with vomiting or diarrhea

If you feel faint or dizzy, lie down and call your doctor right away.

- Kidney problems. Kidney problems may get worse if you already have kidney disease. You may have changes in your kidney test results, and you may need a lower dose of telmisartan and amlodipine tablets. Call your doctor if you get:
  - swelling in your feet, ankles, or hands
  - unexplained weight gain

Call your doctor right away if you get any of the symptoms listed above.

- Heart problems or heart attack. Heart problems may get worse in people that already have heart disease. This may happen when you start telmisartan and amlodipine tablets or when there is an increase in your dose of telmisartan and amlodipine tablets. Get emergency help if you get worse chest pain or chest pain that does not go away.
- High potassium in the blood (hyperkalemia). Your doctor may check your potassium levels as needed.
- Muscle rigidity, tremor and/or abnormal muscle movement.

Rare, serious allergic reactions may happen. Tell your doctor right away if you get any of these symptoms:

- swelling of face, tongue, throat
- difficulty breathing
- skin rash

The most common side effects of telmisartan and amlodipine tablets include:

- swelling in your hands, ankles, or feet
- feeling like your heart is pounding or racing
- flushing or sudden redness of the face and neck
- dizziness
- back pain
- feeling tired or sleepy
- abdominal pain, nausea, or diarrhea
- low blood pressure or a sudden drop in blood pressure with fainting

These are not all the possible side effects of telmisartan and amlodipine tablets. Tell your doctor if you have any side effect that bothers you or that does not go away.

Call your doctor for medical advice about side effects. You may report side effects to FDA at 1-800-FDA-1088.

How should I store Telmisartan and Amlodipine Tablets?

- Store telmisartan and amlodipine tablets at room temperature 68oto 77 oF (20 oto 25 oC).
- Do not remove telmisartan and amlodipine tablets from blisters until right before you take them.
- Keep telmisartan and amlodipine tablets out of the light and away from moisture.

Keep telmisartan and amlodipine tablets and all medicines out of the reach of children. General information about telmisartan and amlodipine tablets

Medicines are sometimes prescribed for purposes other than those listed in a Patient Information leaflet. Do not use telmisartan and amlodipine tablets for a condition for which it was not prescribed. Do not give telmisartan and amlodipine tablets to other people, even if they have the same symptoms that you have. It may harm them.

This Patient Information leaflet summarizes the most important information about telmisartan and amlodipine tablets. If you would like more information, talk with your doctor. You can ask your pharmacist or doctor for information about telmisartan and amlodipine tablets that is written for health professionals.

For more information, go to www.lupinpharmaceuticals.com or call Lupin Pharmaceuticals, Inc. at 1- 800-399-2561.

What are the ingredients in Telmisartan and Amlodipine Tablets?

Active ingredients: telmisartan and amlodipine besylate

Inactive ingredients: colloidal silicon dioxide, crosscarmellose sodium, ferric oxide red, ferric oxide yellow, mannitol, magnesium stearate, povidone, sodium hydroxide and sodium starch glycolate.

What is high blood pressure (hypertension)?

Blood pressure is the force in your blood vessels when your heart beats and when your heart rests. You have high blood pressure when the force is too much. Telmisartan and amlodipine tablets can help your blood vessels relax so your blood pressure is lower. Medicines that lower your blood pressure lower your chance of having a stroke or heart attack.

High blood pressure makes the heart work harder to pump blood throughout the body and causes damage to the blood vessels. If high blood pressure is not treated, it can lead to stroke, heart attack, heart failure, kidney failure, and vision problems.

How to open the blister:

1. Tear (You may also use scissors to tear the blister apart)

2. Peel (Peel off the paper layer from the aluminum foil)

3. Push (Push the tablet through the foil)

This Patient Information has been approved by the U.S. Food and Drug Administration.

® The brands listed are trademarks of their respective owners and are not trademarks of Lupin Pharmaceuticals, Inc. The makers of these brands are not affiliated with and do not endorse Lupin Pharmaceuticals, Inc. or its products.

Manufactured for:

Lupin Pharmaceuticals, Inc.

Baltimore, Maryland 21202

United States

Manufactured by:

Lupin Limited

Goa 403 722 INDIA

Revised: May 2018 ID#: 254923

PRINCIPAL DISPLAY PANEL

TELMISARTAN AND AMLODIPINE TABLETS

Rx Only

40 mg/5 mg

NDC 68180-196-06

A Bottle of 30 tablets

TELMISARTAN AND AMLODIPINE TABLETS

Rx Only

40 mg/10 mg

NDC 68180-197-06

A Bottle of 30 tablets

TELMISARTAN AND AMLODIPINE TABLETS

Rx Only

80 mg/5 mg

NDC 68180-198-06

A Bottle of 30 tablets

TELMISARTAN AND AMLODIPINE TABLETS

Rx Only

80 mg/10 mg

NDC 68180-199-06

A Bottle of 30 tablets